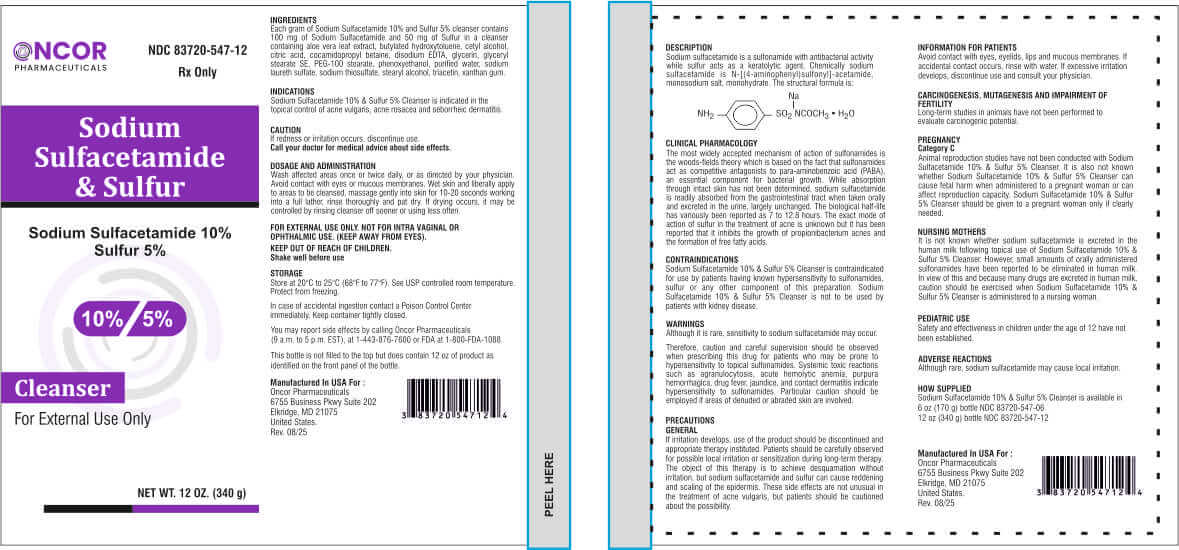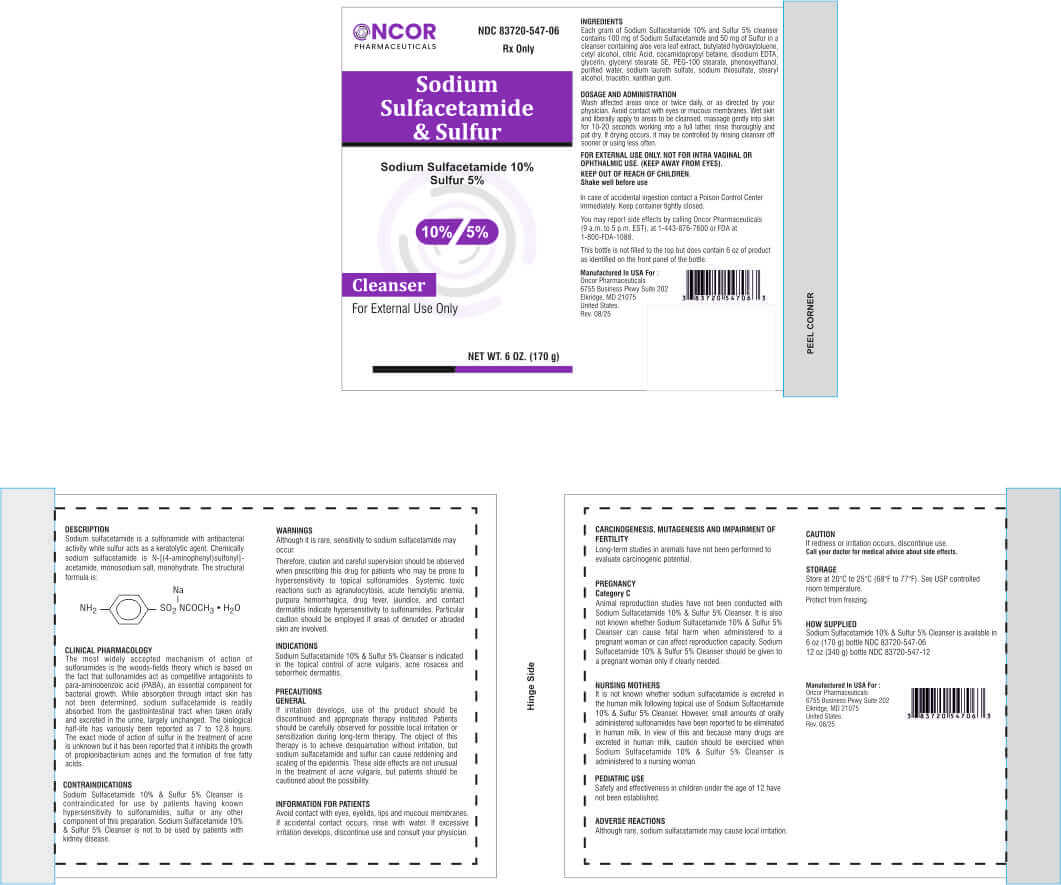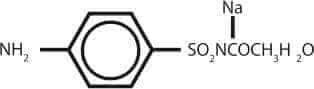 DRUG LABEL: Sodium Sulfacetamide 10% and Sulfur 5% Cleanser
NDC: 83720-547 | Form: RINSE
Manufacturer: Oncor Pharmaceuticals
Category: prescription | Type: HUMAN PRESCRIPTION DRUG LABEL
Date: 20260211

ACTIVE INGREDIENTS: SULFACETAMIDE SODIUM 100 mg/1 g; SULFUR 50 mg/1 g
INACTIVE INGREDIENTS: ALOE VERA LEAF; BUTYLATED HYDROXYTOLUENE; CETYL ALCOHOL; CITRIC ACID; COCAMIDOPROPYL BETAINE; EDETATE DISODIUM; GLYCERIN; GLYCERYL STEARATE SE; PEG-100 STEARATE; PHENOXYETHANOL; WATER; SODIUM LAURETH SULFATE; SODIUM THIOSULFATE; STEARYL ALCOHOL; TRIACETIN; XANTHAN GUM

Sodium Sulfacetamide 10% and Sulfur 5% Cleanser

Rx Only DESCRIPTION

Each gram of sodium sulfacetamide 10% and sulfur 5% cleanser contains 100 mg of sodium sulfacetamide and 50 mg of sulfur in a cleanser containing Aloe vera leaf extract, Butylated hydroxytoluene, Cetyl alcohol, Citric acid, Cocamidopropyl betaine, Disodium EDTA, Glycerin, Glyceryl stearate SE, PEG-100 stearate, Phenoxyethanol, Purified water, Sodium laureth sulfate, Sodium thiosulfate, Stearyl alcohol, Triacetin, Xanthan gum.

Sodium sulfacetamide is a sulfonamide with antibacterial activity while sulfur acts as a keratolytic agent. Chemically sodium sulfacetamide is N-[(4-aminophenyl)sulfonyl]-acetamide, monosodium salt, monohydrate. The structural formula is:

INDICATIONS

Sodium Sulfacetamide 10% & Sulfur 5% Cleanser is indicated in the topical control of acne vulgaris, acne rosacea and seborrheic dermatitis.

DOSAGE AND ADMINISTRATION

Wash affected areas once or twice daily, or as directed by your physician. Avoid contact with eyes or mucous membranes. Wet skin and libera ly apply to areas to be cleansed, massage gently into skin for 10-20 seconds working into a full lather, rinse thoroughly and pat dry. If drying occurs, it may be contro led by rinsing cleanser off sooner or using less often.

CAUTION

If redness or irritaiton occurs, discontinue use.
Call your doctor for medical advice about side effects.

FOR EXTERNAL USE ONLY. NOT FOR INTRA VAGINAL OR OPHTHALMIC USE. (KEEP AWAY FROM EYES).

KEEP OUT OF REACH OF CHILDREN.
Shake well before use

STORAGE

Store at 20°C to 25°C (68°F to 77°F). See USP controlled room temperature.

Protect from freezing.

CLINICAL PHARMACOLOGY

The most widely accepted mechanism of action of sulfonamides is the woods-fields theory which is based on the fact that sulfonamides act as competitive antagonists to para-aminobenzoic acid (PABA), an essential component for bacterial growth. While absorption through intact skin has not been determined, sodium sulfacetamide is readily absorbed from the gastrointestinal tract when taken orally and excreted in the urine, largely unchanged. The biological half-life has variously been reported as 7 to 12.8 hours. The exact mode of action of sulfur in the treatment of acne is unknown but it has been reported that it inhibits the growth of propionibacterium acnes and the formation of free fatty acids.

CONTRAINDICATIONS

Sodium Sulfacetamide 10% & Sulfur 5% Cleanser is contraindicated for use by patients having known hypersensitivity to sulfonamides, sulfur or any other component of this preparation. Sodium Sulfacetamide 10% & Sulfur 5% Cleanser is not to be used by patients with kidney disease.

WARNINGS

Although it is rare, sensitivity to sodium sulfacetamide may occur.

Therefore, caution and careful supervision should be observed when prescribing this drug for patients who may be prone to hypersensitivity to topical sulfonamides. Systemic toxic reactions such as agranulocytosis, acute hemolytic anemia, purpura hemorrhagica, drug fever, jaundice, and contact dermatitis indicate hypersensitivity to sulfonamides. Particular caution should be employed if areas of denuded or abraded skin are involved.

PRECAUTIONS GENERAL

If irritation develops, use of the product should be discontinued and appropriate therapy instituted. Patients should be carefully observed for possible local irritation or sensitization during long-term therapy. The object of this therapy is to achieve desquamation without irritation, but sodium sulfacetamide and sulfur can cause reddening and scaling of the epidermis. These side effects are not unusual in the treatment of acne vulgaris, but patients should be cautioned about the possibility.

INFORMATION FOR PATIENTS

Avoid contact with eyes, eyelids, lips and mucous membranes. If accidental contact occurs, rinse with water. If excessive irritation develops, discontinue use and consult your physician.

CARCINOGENESIS, MUTAGENESIS AND IMPAIRMENT OF FERTILITY

Long-term studies in animals have not been performed to evaluate carcinogenic potential.

PREGNANCY Category C

Animal reproduction studies have not been conducted with Sodium Sulfacetamide 10% & Sulfur 5% Cleanser. It is also not known whether Sodium Sulfacetamide 10% & Sulfur 5% Cleanser can cause fetal harm when administered to a pregnant woman or can affect reproduction capacity. Sodium Sulfacetamide 10% & Sulfur 5% Cleanser should be given to a pregnant woman only if clearly needed.

NURSING MOTHERS

It is not known whether sodium sulfacetamide is excreted in the human milk following topical use of Sodium Sulfacetamide 10% & Sulfur 5% Cleanser. However, small amounts of orally administered sulfonamides have milk. In view of this and because many drugs are excreted in human milk, caution should be exercised when Sodium Sulfacetamide 10% & Sulfur 5% Cleanser is administered to a nursing woman.

PEDIATRIC USE

Safety and effectiveness in children under the age of 12 have not been established.

undefined

Although rare, sodium sulfacetamide may cause local irritation.

HOW SUPPLIED

Sodium Sulfacetamide 10% & Sulfur 5% Cleanser is available in
6 oz (170 g) bottle NDC 83720-547-06
12 oz (340 g) bottle NDC 83720-547-12

In case of accidental ingestion contact a Poison Control Center immediately. Keep container tightly closed.

You may report side effects by ca ling Oncor Pharmaceuticals (9 a.m. to 5 p.m. EST), at 1-443-876-7600 or FDA at 1-800-FDA-1088.

PACKAGE LABEL

Manufactured In USA For :

Oncor Pharmaceuticals
6755 Business Pkwy Suite 202
Elkridge, MD 21075
United States.
Rev. 08/25